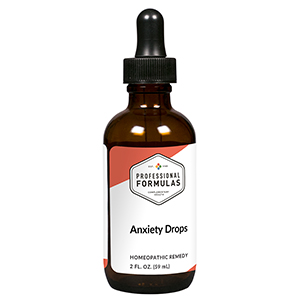 DRUG LABEL: Anxious Drops
NDC: 63083-2098 | Form: LIQUID
Manufacturer: Professional Complementary Health Formulas
Category: homeopathic | Type: HUMAN OTC DRUG LABEL
Date: 20190815

ACTIVE INGREDIENTS: SODIUM BORATE 4 [hp_X]/59 mL; SODIUM CHLORIDE 4 [hp_X]/59 mL; ASTRAGALUS AMERICANUS WHOLE 6 [hp_X]/59 mL; CAUSTICUM 6 [hp_X]/59 mL; ELETTARIA ENSAL WHOLE 6 [hp_X]/59 mL; LEAD 12 [hp_X]/59 mL; SEPIA OFFICINALIS JUICE 12 [hp_X]/59 mL; STRYCHNOS IGNATII SEED 12 [hp_X]/59 mL; GELSEMIUM SEMPERVIRENS ROOT 12 [hp_X]/59 mL; LILIUM LANCIFOLIUM WHOLE FLOWERING 30 [hp_X]/59 mL
INACTIVE INGREDIENTS: ALCOHOL; WATER

C98

ACTIVE INGREDIENTS

Borax 4X
Natrum muriaticum 4X
Astragalus 6X
Causticum 6X
Elettaria cardamomum 6X
Plumbum metallicum 12X
Sepia 12X
Ignatia amara 12X, 30X
Gelsemium sempervirens 12X, 30X, 60X
Lilium tigrinum 30X

QUESTIONS

Professional Formulas

PO Box 2034 Lake Oswego, OR 97035

INDICATIONS

For the temporary relief of anxiousness, restlessness, racing thoughts, excessive worry, poor concentration, or stress.*

PURPOSE

*Claims based on traditional homeopathic practice, not accepted medical evidence. Not FDA evaluated.

WARNINGS

In case of overdose, get medical help or contact a poison control center right away.

Keep out of the reach of children.

PREGNANCY OR BREAST FEEDING

If pregnant or breastfeeding, ask a healthcare professional before use.

DIRECTIONS

Place drops under tongue 30 minutes before/after meals. Adults and children 12 years and over: Take 10 drops up to 3 times per day for up to 6 weeks. For immediate onset of symptoms, take 10 to 15 drops every 15 minutes up to 3 hours. For less severe symptoms, take 10-15 drops hourly up to 8 hours. Consult a physician for use in children under 12 years of age.

OTHER INFORMATION

Tamper resistant. If seal is broken, do not use. After opening, close container tightly and store at room temperature away from heat.

INACTIVE INGREDIENTS

20% ethanol, purified water.

LABEL

Est 1985

Professional Formulas

Complementary Health

Anxious Drops

Homeopathic Remedy

2 FL. OZ. (59 mL)